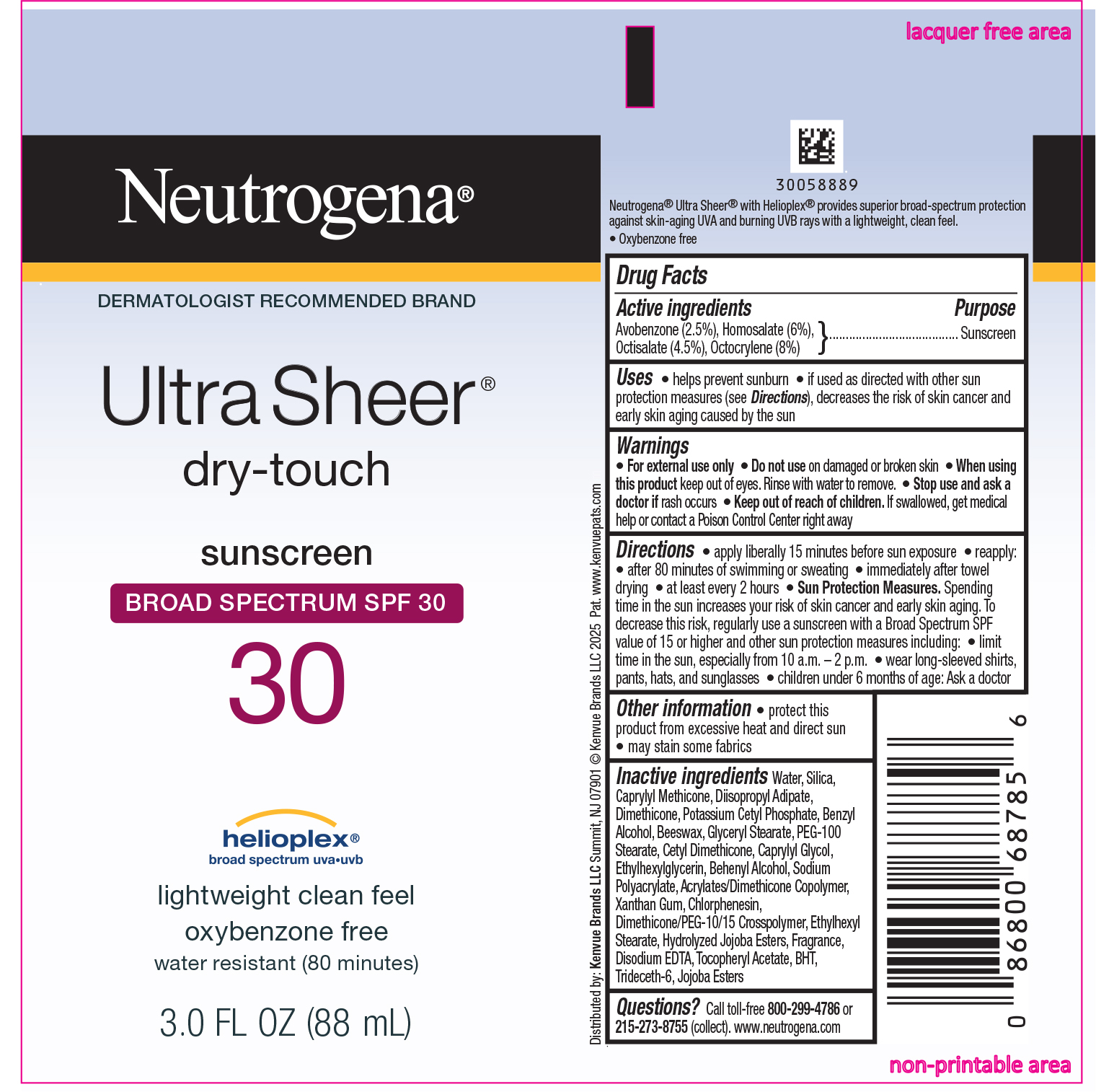 DRUG LABEL: Neutrogena Ultra Sheer Dry Touch Sunscreen Broad Spectrum SPF 30
NDC: 69968-0552 | Form: LOTION
Manufacturer: Kenvue Brands LLC
Category: otc | Type: HUMAN OTC DRUG LABEL
Date: 20250821

ACTIVE INGREDIENTS: AVOBENZONE 25 mg/1 mL; HOMOSALATE 60 mg/1 mL; OCTISALATE 45 mg/1 mL; OCTOCRYLENE 80 mg/1 mL
INACTIVE INGREDIENTS: DIMETHICONE/PEG-10/15 CROSSPOLYMER; CAPRYLYL GLYCOL; ETHYLHEXYLGLYCERIN; DOCOSANOL; 2-ETHYLHEXYL ACRYLATE, METHACRYLATE, METHYL METHACRYLATE, OR BUTYL METHACRYLATE/HYDROXYPROPYL DIMETHICONE COPOLYMER (30000-300000 MW); XANTHAN GUM; CHLORPHENESIN; ETHYLHEXYL STEARATE; HYDROLYZED JOJOBA ESTERS (ACID FORM); EDETATE DISODIUM ANHYDROUS; .ALPHA.-TOCOPHEROL ACETATE; BUTYLATED HYDROXYTOLUENE; TRIDECETH-6; JOJOBA OIL, RANDOMIZED; SILICON DIOXIDE; CAPRYLYL TRISILOXANE; DIISOPROPYL ADIPATE; DIMETHICONE; POTASSIUM CETYL PHOSPHATE; WATER; BENZYL ALCOHOL; YELLOW WAX; GLYCERYL MONOSTEARATE; PEG-100 STEARATE; CETYL DIMETHICONE 25

Neutrogena® Ultra Sheer® dry-touch sunscreen BROAD SPECTRUM SPF 30

Drug Facts

ACTIVE INGREDIENT

Active ingredients | Purpose
Avobenzone 2.5% | Sunscreen
Homosalate 6% | Sunscreen
Octisalate 4.5% | Sunscreen
Octocrylene 8% | Sunscreen

Uses

- helps prevent sunburn
- if used as directed with other sun protection measures (see Directions), decreases the risk of skin cancer and early skin aging caused by the sun

Warnings

- For external use only

- Do not use on damaged or broken skin

When using this product

keep out of eyes. Rinse with water to remove.

- Stop use and ask a doctor if rash occurs

- Keep out of reach of children. If swallowed, get medical help or contact a Poison Control Center right away

Directions

- apply liberally 15 minutes before sun exposure
- reapply:
- after 80 minutes of swimming or sweating
- immediately after towel drying
- at least every 2 hours
- Sun Protection Measures. Spending time in the sun increases your risk of skin cancer and early skin aging. To decrease this risk, regularly use a sunscreen with a Broad Spectrum SPF value of 15 or higher and other sun protection measures including:
- limit time in the sun, especially from 10 a.m. – 2 p.m.
- wear long-sleeved shirts, pants, hats, and sunglasses
- children under 6 months of age: Ask a doctor

Other information

- protect this product from excessive heat and direct sun
- may stain some fabrics

Inactive ingredients

Water, Silica, Caprylyl Methicone, Diisopropyl Adipate, Dimethicone, Potassium Cetyl Phosphate, Benzyl Alcohol, Beeswax, Glyceryl Stearate, PEG-100 Stearate, Cetyl Dimethicone, Caprylyl Glycol, Ethylhexylglycerin, Behenyl Alcohol, Sodium Polyacrylate, Acrylates/Dimethicone Crosspolymer, Xanthan Gum, Chlorphenesin, Dimethicone/PEG-10/15 Crosspolymer, Ethylhexyl Stearate, Hydrolyzed Jojoba Esters, Fragrance, Disodium EDTA, Tocopheryl Acetate, BHT, Trideceth-6, Jojoba Esters

Questions or Comments?

Call toll-free 800-299-4786 or 215-273-8755 (collect). www.neutrogena.com

Distributed by:
Kenvue Brands LLC
Summit, NJ 07901

PRINCIPAL DISPLAY PANEL - 88 mL Tube Label

Neutrogena®

DERMATOLOGIST RECOMMENDED BRAND

Ultra Sheer®

dry-Touch

sunscreen

BROAD SPECTRUM SPF 30

30

helioplex®

broad spectrum uva.uvb

lightweight clean feel

oxybenzone free

water resistant (80 minutes)

3.0 FL OZ (88 mL)